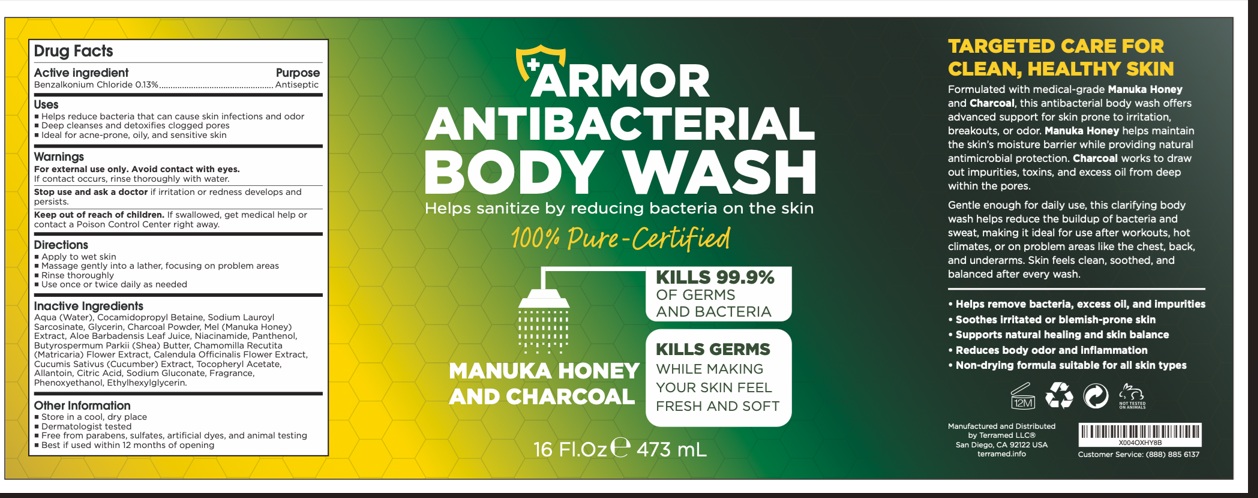 DRUG LABEL: Armor Antibacterial Body Treatment Benzalkonium Chloride
NDC: 83004-028 | Form: LIQUID
Manufacturer: Rida LLC
Category: otc | Type: HUMAN OTC DRUG LABEL
Date: 20250805

ACTIVE INGREDIENTS: BENZALKONIUM CHLORIDE 0.13 g/100 mL
INACTIVE INGREDIENTS: WATER; COCAMIDOPROPYL BETAINE; LOPERAMIDE; GLYCERIN; ACTIVATED CHARCOAL; HONEY; ALOE VERA LEAF JUICE; NIACINAMIDE; PANTHENOL; SHEA BUTTER; CHAMOMILE FLOWER OIL; CALENDULA OFFICINALIS FLOWER; CUCUMBER; .ALPHA.-TOCOPHEROL ACETATE; ALLANTOIN; CITRIC ACID MONOHYDRATE; SODIUM GLUCONATE; PHENOXYETHANOL; ETHYLHEXYLGLYCERIN

ARMOR ANTIBACTERIAL BODY TREATMENT BENZALKONIUM CHLORIDE

Drug Facts

Active ingredient

Benzalkonium Chloride (0.13%)

Purpose

Antiseptic

Uses

- Helps reduce bacteria that can cause skin infections and odor
- Deeply cleanses and detoxifies clogged pores
- Ideal for acne-prone, oily, and sensitive skin

Warnings

For external use only. Avoid contact with eyes. If contact occurs, rinse thoroughly with water

Stop use and ask a doctorif irritation or redness develops and persists

Keep out of reach of children. If swallowed, get medical help or contact a Poison Control Center right away

Directions

- Apply to wet skin
- Massage gently into a lather, focusing on problem areas
- Rinse thoroughly
- Use once or twice daily as needed

Inactive ingredients

Water (Aqua), Cocamidopropyl Betaine, Sodium Lauroyl Sarcosinate, Glycerin, Charcoal Powder, Mel (Honey), Aloe Barbadensis Leaf Juice, Niacinamide, Panthenol, Butyrospermum Parkii (Shea) Butter, Chamomilla Recutita Flower Extract, Calendula Officinalis Extract, Cucumis Sativus (Cucumber) Fruit Extract, Tocopheryl Acetate, Allantoin, Citric Acid, Sodium Gluconate, Phenoxyethanol, Ethylhexylglycerin

Questions?

- Store in a cool, dry place
- Dermatologist tested
- Free from parabens, sulfates, artificial dyes, and animal testing
- Best if used within 12 months of opening